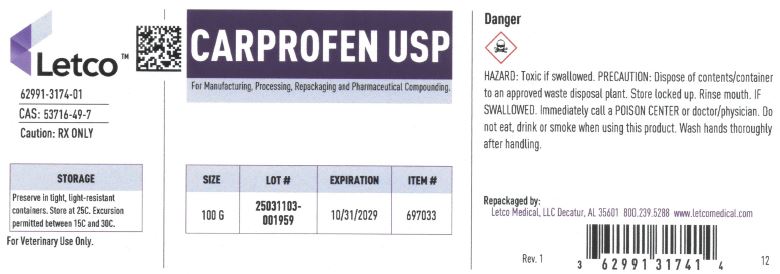 DRUG LABEL: Carprofen
NDC: 62991-3174 | Form: POWDER
Manufacturer: LETCO MEDICAL, LLC
Category: other | Type: BULK INGREDIENT - ANIMAL DRUG
Date: 20250627

ACTIVE INGREDIENTS: CARPROFEN 1 g/1 g

Carprofen USP

PACKAGE LABEL

Carprofen USP 100g